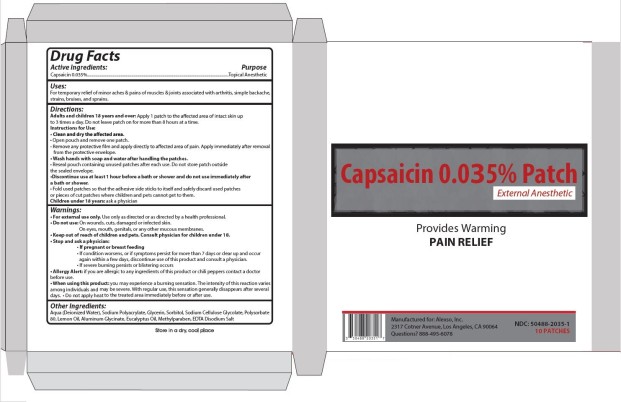 DRUG LABEL: Capsaicin 0.035 Percent
NDC: 50488-2035 | Form: PATCH
Manufacturer: Alexso, Inc
Category: otc | Type: HUMAN OTC DRUG LABEL
Date: 20250701

ACTIVE INGREDIENTS: CAPSAICIN 0.035 g/100 g
INACTIVE INGREDIENTS: WATER; GLYCERIN; SORBITOL; CARBOXYMETHYLCELLULOSE SODIUM; POLYSORBATE 80; LEMON OIL; ALUMINUM GLYCINATE; EUCALYPTUS OIL; METHYLPARABEN; EDETATE DISODIUM; SODIUM POLYACRYLATE (8000 MW)

Capsaicin 0_035 Percent Patch

CAPSAICIN – Capsaicin 0.035% Patch

Alexso, Inc.

Disclaimer: Most OTC drugs are not reviewed and approved by FDA, however they may be marketed if they comply with applicable regulations and policies. FDA has not evaluated whether this product complies.

----------

Capsaicin 0.035% Patch

Drug Facts

Active ingredient

Capsaicin 0.035%

Purpose

External analgesic

Uses

Temporarily relieves minor aches and pains of muscles and joints due to:

• arthritis

• simple backache

• strains

• bruises

• sprains

Warnings

For external use only. Use only as directed or as directed by a health care professional

Read all warnings and directions before use.

Discontinue use at least one hour prior to bath, shower, or swimming; do not use immediately after bath, shower, or swimming.

Do not use

• On wounds, cuts, damaged or infected skin

• On eyes, mouth, genitals, or any other mucous membranes

Allergy Alert: if you are allergic to capsicum or chili peppers or any inactive ingredient of this product, contact a doctor before use.

When using this product

• You may experience a burning sensation. The intensity of this reaction varies among individuals and may be severe. With regular use, this sensation generally disappears after several days.

• Avoid contact with the eyes, lips, nose and mucous membranes

• Do not tightly wrap or bandage the treated area

• Do not apply heat to the treated area immediately before or after use

Stop use and ask a physician:

• If pregnant or breast feeding

• If condition worsens, or if symptoms persist for more than 7 days or clear up and occur again within a few days, discontinue use of this product and consult a physician.

• If severe burning persists or blistering occurs

Keep out of reach of children and pets.

If swallowed, get medical help or contact a Poison Control Center immediately.

Directions

Adults and children 18 years of age and older:

Apply 1 patch to the affected area of intact skin up to 3 times a day. Do not leave patch on for more than 8 hours at a time.

- Clean and dry the affected area.

- Open pouch and remove one patch.

- Remove any protective film and apply directly to affected area of pain. Apply immediately after removal from the protective envelope.

- Wash hands with soap and water after handling the patches.

- Reseal pouch containing unused patches after each use. Do not store patch outside the sealed envelope.

- Fold used patches so that the adhesive side sticks to itself and safely discard used patches or pieces of cut patches where children and pets cannot get to them.

Children under 18 years: Ask a physician

Other information

Store at room temperature 15°-30°C (59°-86°F)

Inactive ingredients

Aqua (Deionized Water), Sodium Polyacrylate, Glycerin, Sorbitol, Sodium Cellulose Glycolate, Polysorbate 80, Lemon Oil, Aluminum Glycinate, Eucalyptus Oil, Methylparaben, EDTA Disodium Salt

PRINCIPAL DISPLAY PANEL

Capsaicin 0.035% Patch

NDC 50488-2035-1

10 Patches (5 per Resealable Pouch)

Alexso, Inc